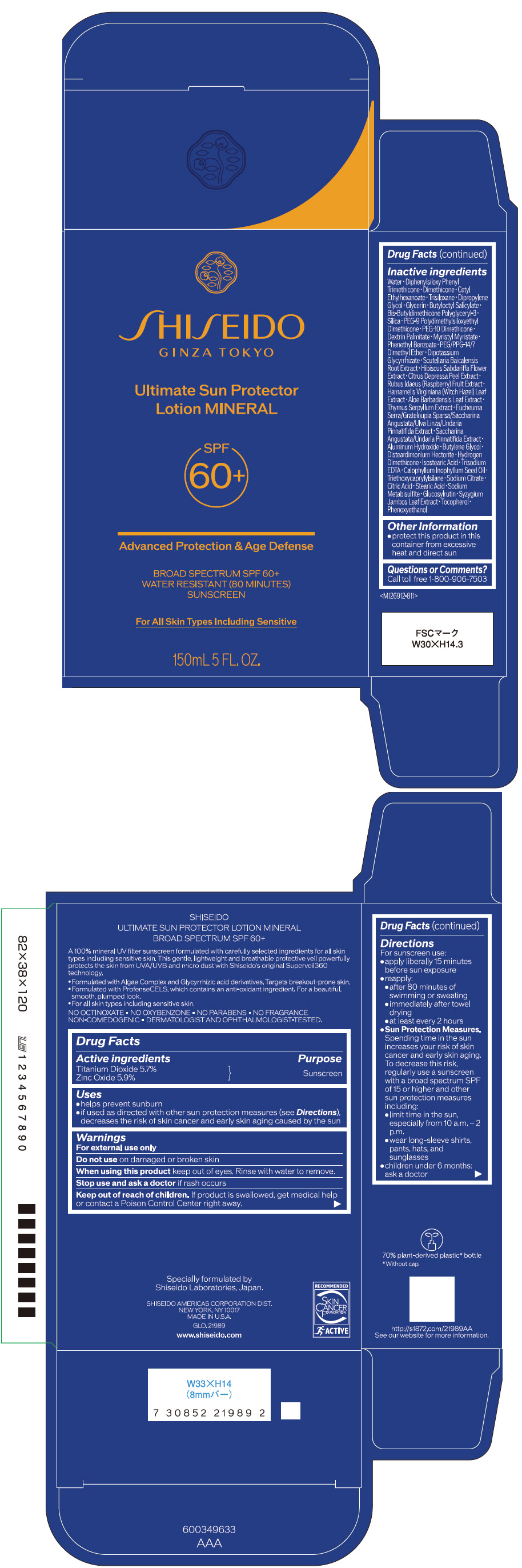 DRUG LABEL: SHISEIDO ULTIMATE SUN PROTECTOR MINERAL
NDC: 58411-903 | Form: LOTION
Manufacturer: SHISEIDO AMERICAS CORPORATION
Category: otc | Type: HUMAN OTC DRUG LABEL
Date: 20260223

ACTIVE INGREDIENTS: TITANIUM DIOXIDE 9.44 g/150 mL; ZINC OXIDE 9.77 g/150 mL
INACTIVE INGREDIENTS: WATER; DIPHENYLSILOXY PHENYL TRIMETHICONE; DIMETHICONE; CETYL ETHYLHEXANOATE; TRISILOXANE; DIPROPYLENE GLYCOL; GLYCERIN; BUTYLOCTYL SALICYLATE; SILICON DIOXIDE; PEG-10 DIMETHICONE (600 CST); DEXTRIN PALMITATE (CORN; 20000 MW); MYRISTYL MYRISTATE; PHENETHYL BENZOATE; PEG/PPG-14/7 DIMETHYL ETHER; GLYCYRRHIZINATE DIPOTASSIUM; SCUTELLARIA BAICALENSIS ROOT; HIBISCUS SABDARIFFA FLOWER; TANGERINE PEEL; RASPBERRY; HAMAMELIS VIRGINIANA LEAF; ALOE VERA LEAF; THYMUS SERPYLLUM WHOLE; ALUMINUM HYDROXIDE; BUTYLENE GLYCOL; DISTEARDIMONIUM HECTORITE; HYDROGEN DIMETHICONE (13 CST); ISOSTEARIC ACID; EDETATE TRISODIUM; CALOPHYLLUM INOPHYLLUM WHOLE; TRIETHOXYCAPRYLYLSILANE; MONOSODIUM CITRATE; CITRIC ACID MONOHYDRATE; STEARIC ACID; SODIUM METABISULFITE; .ALPHA.-TOCOPHEROL; PHENOXYETHANOL

SHISEIDO ULTIMATE SUN PROTECTOR LOTION MINERAL

Drug Facts

ACTIVE INGREDIENT

Active ingredients | Purpose
TITANIUM DIOXIDE 5.7% | Sunscreen
ZINC OXIDE 5.9% | Sunscreen

Uses

- helps prevent sunburn
- if used as directed with other sun protection measures (see Directions), decreases the risk of skin cancer and early skin aging caused by the sun

Warnings

For external use only

Do not useon damaged or broken skin

WHEN USING

When using this productkeep out of eyes. Rinse with water to remove.

Stop use and ask a doctorif rash occurs.

Keep out of reach of children.If product is swallowed, get medical help or contact a Poison Control Center right away.

Directions

For sunscreen use:

- apply liberally 15 minutes before sun exposure
- use a water resistant sunscreen if swimming or sweating
- reapply at least every 2 hours
- Sun Protection Measures. Spending time in the sun increases your risk of skin cancer and early skin aging. To decrease this risk, regularly use a sunscreen with a Broad Spectrum SPF of 15 or higher and other sun protection measures including:
  - limit time in the sun, especially from 10 a.m. – 2 p.m.
  - wear long-sleeve shirts, pants, hats, and sunglasses
- children under 6 months: Ask a doctor

Inactive Ingredients

WATER･DIPHENYLSILOXY PHENYL TRIMETHICONE･DIMETHICONE･CETYL ETHYLHEXANOATE･TRISILOXANE･DIPROPYLENE GLYCOL･GLYCERIN･BUTYLOCTYL SALICYLATE･BIS-BUTYLDIMETHICONE POLYGLYCERYL-3･SILICA･PEG-9 POLYDIMETHYLSILOXYETHYL DIMETHICONE･PEG-10 DIMETHICONE･DEXTRIN PALMITATE･MYRISTYL MYRISTATE･PHENETHYL BENZOATE･PEG/PPG-14/7 DIMETHYL ETHER･DIPOTASSIUM GLYCYRRHIZATE･SCUTELLARIA BAICALENSIS ROOT EXTRACT･HIBISCUS SABDARIFFA FLOWER EXTRACT･CITRUS DEPRESSA PEEL EXTRACT･RUBUS IDAEUS (RASPBERRY) FRUIT EXTRACT･HAMAMELIS VIRGINIANA (WITCH HAZEL) LEAF EXTRACT･ALOE BARBADENSIS LEAF EXTRACT･THYMUS SERPYLLUM EXTRACT･EUCHEUMA SERRA/GRATELOUPIA SPARSA/SACCHARINA ANGUSTATA/ULVA LINZA/UNDARIA PINNATIFIDA EXTRACT･SACCHARINA ANGUSTATA/UNDARIA PINNATIFIDA EXTRACT･ALUMINUM HYDROXIDE･BUTYLENE GLYCOL･DISTEARDIMONIUM HECTORITE･HYDROGEN DIMETHICONE･ISOSTEARIC ACID･TRISODIUM EDTA･CALOPHYLLUM INOPHYLLUM SEED OIL･TRIETHOXYCAPRYLYLSILANE･SODIUM CITRATE･CITRIC ACID･STEARIC ACID･SODIUM METABISULFITE･GLUCOSYLRUTIN･SYZYGIUM JAMBOS LEAF EXTRACT･TOCOPHEROL･PHENOXYETHANOL･

Other information

- protect this product in this container from excessive heat and direct sun.

Questions or comments?

Call toll free 1-800-906-7503

PRINCIPAL DISPLAY PANEL - 150 mL Container Carton

SHISEIDO
GINZA TOKYO

Ultimate Sun Protector
Lotion MINERAL

SPF
60+

Advanced Protection & Age Defense

BROAD SPECTRUM SPF 60+
WATER RESISTANT (80 MINUTES)
SUNSCREEN

For All Skin Types Including Sensitive

150mL 5 FL. OZ.